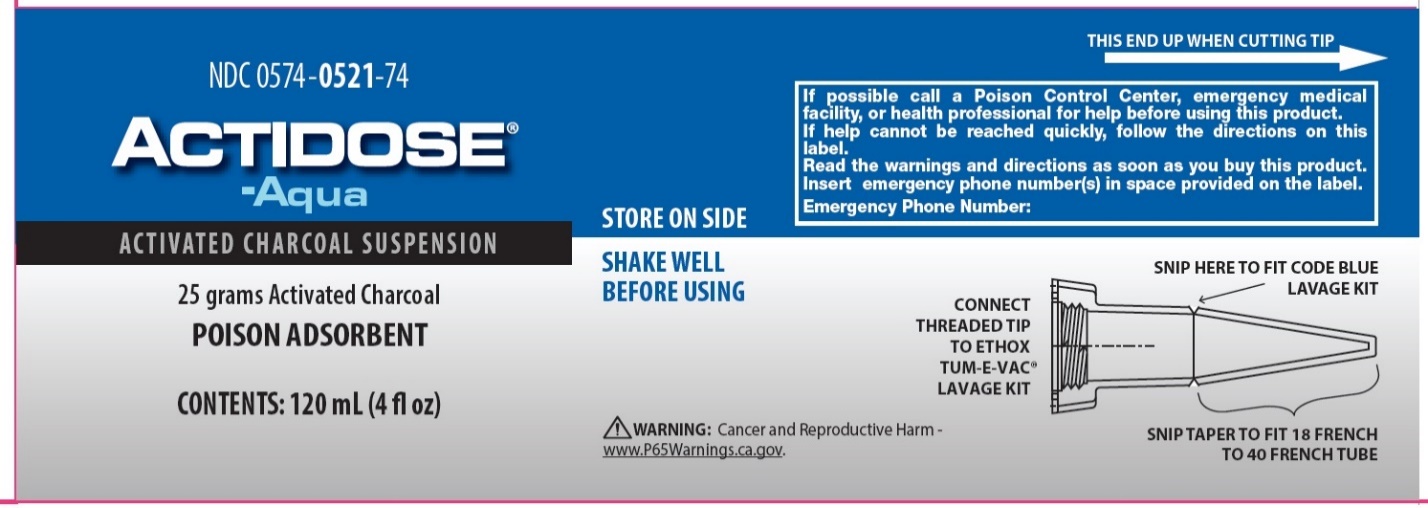 DRUG LABEL: ACTIDOSE AQUA
NDC: 0574-0521 | Form: SUSPENSION
Manufacturer: Padagis US LLC
Category: otc | Type: HUMAN OTC DRUG LABEL
Date: 20250531

ACTIVE INGREDIENTS: ACTIVATED CHARCOAL 208 mg/1 mL
INACTIVE INGREDIENTS: ANHYDROUS CITRIC ACID; GLYCERIN; PROPYLENE GLYCOL; SUCROSE; WATER

ACTIDOSE®-Aqua Drug Facts

Active ingredient (in each tube)

Activated Charcoal

Purpose

Poison Adsorbent

Uses

- For emergency use to adsorb swallowed poisons.

Warnings

- Do not give activated charcoal until after the patient has vomited unless directed by a health professional.
- Do not use in persons who are not fully conscious.
- Do not use this product, unless directed by a health professional, if turpentine, corrosives (such as alkalies (lye) and strong acids), or petroleum distillates (such as kerosene, gasoline, paint thinner, cleaning fluid, or furniture polish), have been ingested.

Directions

Oral Dosage: 20 to 30 grams of activated charcoal in a minimum of 8 ounces of liquid or as directed by a health professional. Repeat dose immediately, if possible.

- Shake well
- Snip tapered tip as indicated in drawing and remove. Holding the tube upright, carefully cut off tube closure. Reattach tapered tip and connect to any charcoal administration set or squeeze contents in a cup with a minimum of 4 ounces of liquid for patient to drink.
- If previous attempts to contact a poison control center, emergency medical facility, or health professional were unsuccessful, continue trying.
- Keep patient active and moving.
- Save the container of poison.

Other information

- Store at 20-25°C (68-77°F) [see USP Controlled Room Temperature]. Do not refrigerate.

Inactive Ingredients

Citric acid, glycerin, propylene glycol, sucrose, and water.

Questions?

Please call 1-866-634-9120

Package/Label Principal Display Panel

NDC 0574-0521-74

ACTIDOSE®-Aqua

ACTIVATED CHARCOAL SUSPENSION

25 grams Activated Charcoal

POISON ADSORBENT

If possible call a Poison Control Center, emergency medical facility, or health professional for help before using this product. If help cannot be reached quickly, follow directions on this label. Read label warnings and directions upon buying this product. Insert emergency phone number(s) in space provided on the label.

Emergency Phone Number:

WARNING: Cancer and Reproductive Harm – www.P65Warnings.ca.gov.

CONTENTS: 120 mL (4 fl oz)